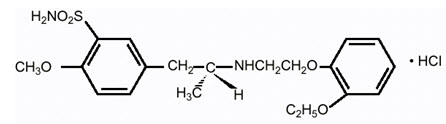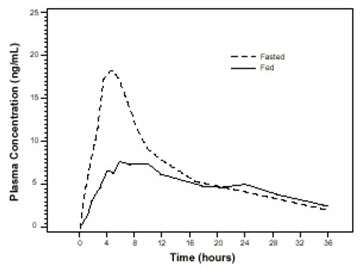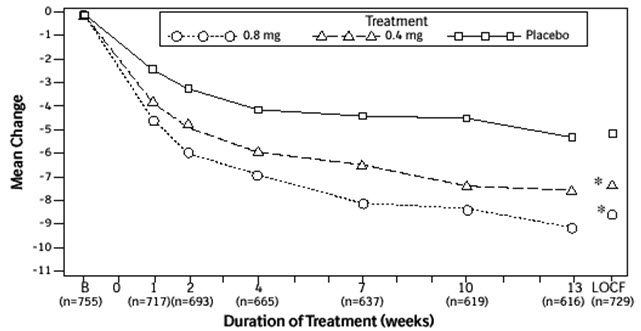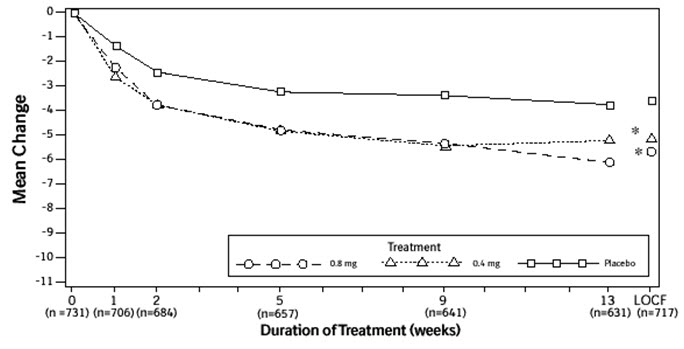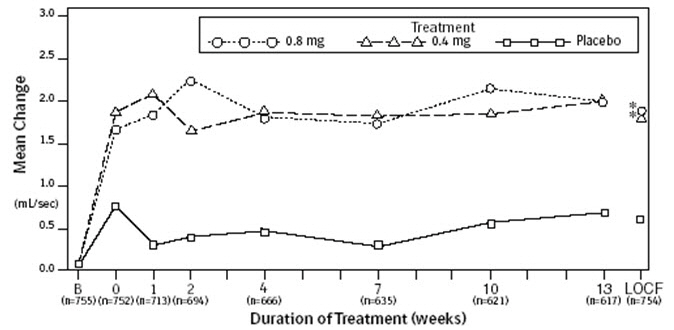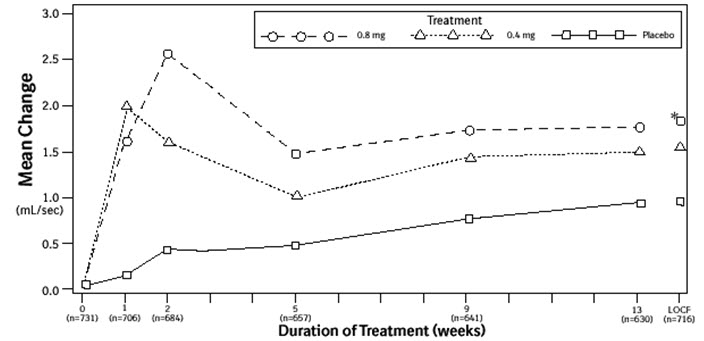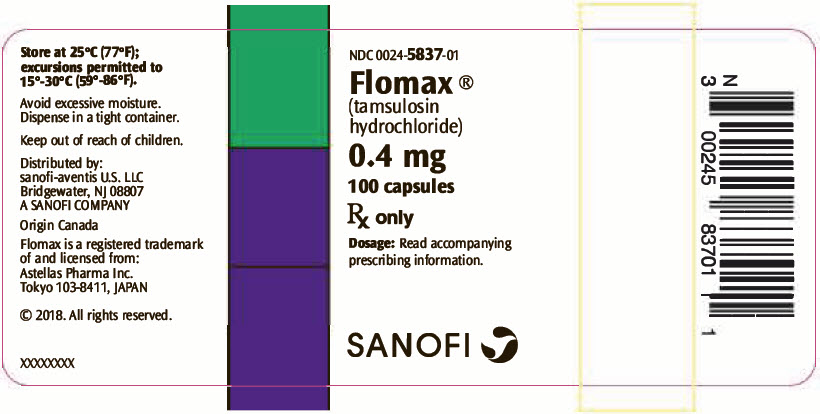 DRUG LABEL: FLOMAX
NDC: 0024-5837 | Form: CAPSULE
Manufacturer: Sanofi-Aventis U.S. LLC
Category: prescription | Type: HUMAN PRESCRIPTION DRUG LABEL
Date: 20250102

ACTIVE INGREDIENTS: TAMSULOSIN HYDROCHLORIDE 0.4 mg/1 1
INACTIVE INGREDIENTS: MICROCRYSTALLINE CELLULOSE; METHACRYLIC ACID AND ETHYL ACRYLATE COPOLYMER; TRIACETIN; CALCIUM STEARATE; TALC; GELATIN, UNSPECIFIED; FERRIC OXIDE RED; FERRIC OXIDE YELLOW; FERROSOFERRIC OXIDE; FD&C BLUE NO. 2; TITANIUM DIOXIDE; PROPYLENE GLYCOL; SHELLAC; POLYSORBATE 80

HIGHLIGHTS OF PRESCRIBING INFORMATION

These highlights do not include all the information needed to use FLOMAX safely and effectively. See full prescribing information for FLOMAX.
FLOMAX® (tamsulosin hydrochloride, USP) capsules, for oral use
Initial U.S. Approval: 1997

1 INDICATIONS AND USAGE

- FLOMAX is an alpha1 adrenoceptor antagonist indicated for treatment of the signs and symptoms of benign prostatic hyperplasia (1)
- FLOMAX capsules are not indicated for the treatment of hypertension (1)

2 DOSAGE AND ADMINISTRATION

- 0.4 mg once daily taken approximately one-half hour following the same meal each day. FLOMAX capsules should not be crushed, chewed or opened. (2)
- Can be increased to 0.8 mg once daily for patients who fail to respond to the 0.4 mg dose after 2 to 4 weeks of dosing (2)
- If discontinued or interrupted for several days, therapy should start again with the 0.4 mg once-daily dose (2)

3 DOSAGE FORMS AND STRENGTHS

- Capsules: 0.4 mg (3)

4 CONTRAINDICATIONS

- Contraindicated in patients known to be hypersensitive to tamsulosin hydrochloride or any component of FLOMAX capsules (4, 6.2)

5 WARNINGS AND PRECAUTIONS

- Advise patients about the possibility of symptoms related to postural hypotension and to avoid situations where injury could result should syncope occur (5.1)
- Should not be used in combination with strong inhibitors of CYP3A4. Use with caution in combination with moderate inhibitors of CYP3A4, with strong or moderate inhibitors of CYP2D6, in patients known to be CYP2D6 poor metabolizers, or in combination with other cytochrome P450 inhibitors. (5.2, 7.1, 12.3)
- Should not be used in combination with other alpha adrenergic blocking agents (5.2, 7.2, 12.3)
- Exercise caution with concomitant administration of warfarin (5.2, 7.4, 12.3)
- Advise patients about the possibility and seriousness of priapism (5.3)
- Intraoperative Floppy Iris Syndrome has been observed during cataract and glaucoma surgery in some patients. Advise patients considering cataract or glaucoma surgery to tell their ophthalmologist that they have taken FLOMAX capsules. (5.5)
- Advise patients to be screened for the presence of prostate cancer prior to treatment and at regular intervals afterwards (5.4)

6 ADVERSE REACTIONS

- The most common adverse events (≥2% of patients and at a higher incidence than placebo) with the 0.4 mg dose or 0.8 mg dose were headache, dizziness, rhinitis, infection, abnormal ejaculation, asthenia, back pain, diarrhea, pharyngitis, chest pain, cough increased, somnolence, nausea, sinusitis, insomnia, libido decreased, tooth disorder, and blurred vision (6.1)

To report SUSPECTED ADVERSE REACTIONS, contact sanofi-aventis U.S. LLC at 1-800-633-1610 or FDA at 1-800-FDA-1088 or www.fda.gov/medwatch.

7 DRUG INTERACTIONS

- FLOMAX capsules 0.4 mg should not be used with strong inhibitors of CYP3A4 (e.g., ketoconazole). FLOMAX capsules should be used with caution in combination with moderate inhibitors of CYP3A4 (e.g., erythromycin), in combination with strong (e.g., paroxetine) or moderate (e.g., terbinafine) inhibitors of CYP2D6, or in patients known to be CYP2D6 poor metabolizers, particularly at a dose higher than 0.4 mg (e.g., 0.8 mg). (5.2, 7.1, 12.3)
- Concomitant use of PDE5 inhibitors with tamsulosin can potentially cause symptomatic hypotension (5.2, 7.3, 12.3)

8 USE IN SPECIFIC POPULATIONS

- Pediatric Use: Not indicated for use in pediatric populations (8.4, 12.3)
- Geriatric Use: No overall differences in efficacy or safety vs younger patients, but greater sensitivity of some older adults cannot be ruled out (8.5, 12.3)
- Renal Impairment: Has not been studied in patients with end-stage renal disease (8.6, 12.3)
- Hepatic Impairment: Has not been studied in patients with severe hepatic impairment (8.7, 12.3)

FULL PRESCRIBING INFORMATION

1 INDICATIONS AND USAGE

FLOMAX (tamsulosin hydrochloride, USP) capsules are indicated for the treatment of the signs and symptoms of benign prostatic hyperplasia (BPH) [see Clinical Studies (14)]. FLOMAX capsules are not indicated for the treatment of hypertension.

2 DOSAGE AND ADMINISTRATION

FLOMAX capsules 0.4 mg once daily is recommended as the dose for the treatment of the signs and symptoms of BPH. It should be administered approximately one-half hour following the same meal each day. FLOMAX capsules should not be crushed, chewed or opened.

For those patients who fail to respond to the 0.4 mg dose after 2 to 4 weeks of dosing, the dose of FLOMAX capsules can be increased to 0.8 mg once daily. FLOMAX capsules 0.4 mg should not be used in combination with strong inhibitors of CYP3A4 (e.g., ketoconazole) [see Warnings and Precautions (5.2)].

If FLOMAX capsules administration is discontinued or interrupted for several days at either the 0.4 mg or 0.8 mg dose, therapy should be started again with the 0.4 mg once-daily dose.

3 DOSAGE FORMS AND STRENGTHS

Capsule: 0.4 mg, olive green and orange hard gelatin, imprinted on one side with Flomax 0.4 mg and on the other side with BI 58.

4 CONTRAINDICATIONS

FLOMAX capsules are contraindicated in patients known to be hypersensitive to tamsulosin hydrochloride or any component of FLOMAX capsules. Reactions have included skin rash, urticaria, pruritus, angioedema, and respiratory symptoms [see Adverse Reactions (6.2)].

5 WARNINGS AND PRECAUTIONS

5.1 Orthostasis

The signs and symptoms of orthostasis (postural hypotension, dizziness, and vertigo) were detected more frequently in FLOMAX capsule-treated patients than in placebo recipients. As with other alpha adrenergic blocking agents there is a potential risk of syncope [see Adverse Reactions (6.1)]. Patients beginning treatment with FLOMAX capsules should be cautioned to avoid situations in which injury could result should syncope occur.

5.2 Drug Interactions

Tamsulosin is extensively metabolized, mainly by CYP3A4 and CYP2D6. FLOMAX capsules 0.4 mg should not be used in combination with strong inhibitors of CYP3A4 (e.g., ketoconazole) [see Drug Interactions (7.1) and Clinical Pharmacology (12.3)]. FLOMAX capsules should be used with caution in combination with moderate inhibitors of CYP3A4 (e.g., erythromycin), in combination with strong (e.g., paroxetine) or moderate (e.g., terbinafine) inhibitors of CYP2D6, in patients known to be CYP2D6 poor metabolizers particularly at a dose higher than 0.4 mg (e.g., 0.8 mg) [see Drug Interactions (7.1) and Clinical Pharmacology (12.3)].

FLOMAX capsules should be used with caution in combination with cimetidine, particularly at a dose higher than 0.4 mg (e.g., 0.8 mg) [see Drug Interactions (7.1) and Clinical Pharmacology (12.3)].

FLOMAX capsules should not be used in combination with other alpha adrenergic blocking agents [see Drug Interactions (7.2) and Clinical Pharmacology (12.3)].

Caution is advised when alpha adrenergic blocking agents including FLOMAX are coadministered with PDE5 inhibitors. Alpha-adrenergic blockers and PDE5 inhibitors are both vasodilators that can lower blood pressure. Concomitant use of these two drug classes can potentially cause symptomatic hypotension [see Drug Interactions (7.3) and Clinical Pharmacology (12.3)].

Caution should be exercised with concomitant administration of warfarin and FLOMAX capsules [see Drug Interactions (7.4) and Clinical Pharmacology (12.3)].

5.3 Priapism

Rarely (probably less than 1 in 50,000 patients), tamsulosin, like other alpha1 antagonists, has been associated with priapism (persistent painful penile erection unrelated to sexual activity). Because this condition can lead to permanent impotence if not properly treated, patients must be advised about the seriousness of the condition.

5.4 Screening for Prostate Cancer

Prostate cancer and BPH frequently coexist; therefore, patients should be screened for the presence of prostate cancer prior to treatment with FLOMAX capsules and at regular intervals afterwards.

5.5 Intraoperative Floppy Iris Syndrome

Intraoperative Floppy Iris Syndrome (IFIS) has been observed during cataract and glaucoma surgery in some patients on or previously treated with alpha1 blockers, including FLOMAX capsules [see Adverse Reactions (6.2)].

Most reports were in patients taking the alpha1 blocker when IFIS occurred, but in some cases, the alpha1 blocker had been stopped prior to surgery. In most of these cases, the alpha1 blocker had been stopped recently prior to surgery (2 to 14 days), but in a few cases, IFIS was reported after the patient had been off the alpha1 blocker for a longer period (5 weeks to 9 months). IFIS is a variant of small pupil syndrome and is characterized by the combination of a flaccid iris that billows in response to intraoperative irrigation currents, progressive intraoperative miosis despite preoperative dilation with standard mydriatic drugs and potential prolapse of the iris toward the phacoemulsification incisions. The patient's ophthalmologist should be prepared for possible modifications to their surgical technique, such as the utilization of iris hooks, iris dilator rings, or viscoelastic substances.

IFIS may increase the risk of eye complications during and after the operation. The benefit of stopping alpha1 blocker therapy prior to cataract or glaucoma surgery has not been established. The initiation of therapy with tamsulosin in patients for whom cataract or glaucoma surgery is scheduled is not recommended.

5.6 Sulfa Allergy

In patients with sulfa allergy, allergic reaction to FLOMAX capsules has been rarely reported. If a patient reports a serious or life-threatening sulfa allergy, caution is warranted when administering FLOMAX capsules.

6 ADVERSE REACTIONS

6.1 Clinical Trials Experience

Because clinical trials are conducted under widely varying conditions, adverse reactions rates observed in the clinical trials of a drug cannot be directly compared to rates in the clinical trials of another drug and may not reflect the rates observed in practice.

The incidence of treatment-emergent adverse events has been ascertained from six short-term U.S. and European placebo-controlled clinical trials in which daily doses of 0.1 to 0.8 mg FLOMAX capsules were used. These studies evaluated safety in 1783 patients treated with FLOMAX capsules and 798 patients administered placebo. Table 1 summarizes the treatment-emergent adverse events that occurred in ≥2% of patients receiving either FLOMAX capsules 0.4 mg or 0.8 mg and at an incidence numerically higher than that in the placebo group during two 13-week U.S. trials (US92-03A and US93-01) conducted in 1487 men.

Table 1: Treatment-Emergent [A treatment-emergent adverse event was defined as any event satisfying one of the following criteria: - The adverse event occurred for the first time after initial dosing with double-blind study medication; - The adverse event was present prior to or at the time of initial dosing with double-blind study medication and subsequently increased in severity during double-blind treatment; or - The adverse event was present prior to or at the time of initial dosing with double-blind study medication, disappeared completely, and then reappeared during double-blind treatment.] Adverse Events Occurring in ≥2% of FLOMAX Capsules or Placebo Patients in Two U.S. Short-Term Placebo-Controlled Clinical Studies
BODY SYSTEM/ ADVERSE EVENT | FLOMAX CAPSULES GROUPS |  | PLACEBO
 | 0.4 mg n=502 | 0.8 mg n=492 | n=493
BODY AS WHOLE
Headache | 97 (19.3%) | 104 (21.1%) | 99 (20.1%)
Infection [Coding preferred terms also include cold, common cold, head cold, flu, and flu-like symptoms.] | 45 (9.0%) | 53 (10.8%) | 37 (7.5%)
Asthenia | 39 (7.8%) | 42 (8.5%) | 27 (5.5%)
Back pain | 35 (7.0%) | 41 (8.3%) | 27 (5.5%)
Chest pain | 20 (4.0%) | 20 (4.1%) | 18 (3.7%)
NERVOUS SYSTEM
Dizziness | 75 (14.9%) | 84 (17.1%) | 50 (10.1%)
Somnolence | 15 (3.0%) | 21 (4.3%) | 8 (1.6%)
Insomnia | 12 (2.4%) | 7 (1.4%) | 3 (0.6%)
Libido decreased | 5 (1.0%) | 10 (2.0%) | 6 (1.2%)
RESPIRATORY SYSTEM
Rhinitis [Coding preferred terms also include nasal congestion, stuffy nose, runny nose, sinus congestion, and hay fever.] | 66 (13.1%) | 88 (17.9%) | 41 (8.3%)
Pharyngitis | 29 (5.8%) | 25 (5.1%) | 23 (4.7%)
Cough increased | 17 (3.4%) | 22 (4.5%) | 12 (2.4%)
Sinusitis | 11 (2.2%) | 18 (3.7%) | 8 (1.6%)
DIGESTIVE SYSTEM
Diarrhea | 31 (6.2%) | 21 (4.3%) | 22 (4.5%)
Nausea | 13 (2.6%) | 19 (3.9%) | 16 (3.2%)
Tooth disorder | 6 (1.2%) | 10 (2.0%) | 7 (1.4%)
UROGENITAL SYSTEM
Abnormal ejaculation | 42 (8.4%) | 89 (18.1%) | 1 (0.2%)
SPECIAL SENSES
Blurred vision | 1 (0.2%) | 10 (2.0%) | 2 (0.4%)

Signs and Symptoms of Orthostasis

In the two U.S. studies, symptomatic postural hypotension was reported by 0.2% of patients (1 of 502) in the 0.4 mg group, 0.4% of patients (2 of 492) in the 0.8 mg group, and by no patients in the placebo group. Syncope was reported by 0.2% of patients (1 of 502) in the 0.4 mg group, 0.4% of patients (2 of 492) in the 0.8 mg group, and 0.6% of patients (3 of 493) in the placebo group. Dizziness was reported by 15% of patients (75 of 502) in the 0.4 mg group, 17% of patients (84 of 492) in the 0.8 mg group, and 10% of patients (50 of 493) in the placebo group. Vertigo was reported by 0.6% of patients (3 of 502) in the 0.4 mg group, 1% of patients (5 of 492) in the 0.8 mg group, and by 0.6% of patients (3 of 493) in the placebo group.

Multiple testing for orthostatic hypotension was conducted in a number of studies. Such a test was considered positive if it met one or more of the following criteria: (1) a decrease in systolic blood pressure of ≥20 mmHg upon standing from the supine position during the orthostatic tests; (2) a decrease in diastolic blood pressure ≥10 mmHg upon standing, with the standing diastolic blood pressure <65 mmHg during the orthostatic test; (3) an increase in pulse rate of ≥20 bpm upon standing with a standing pulse rate ≥100 bpm during the orthostatic test; and (4) the presence of clinical symptoms (faintness, lightheadedness/lightheaded, dizziness, spinning sensation, vertigo, or postural hypotension) upon standing during the orthostatic test.

Following the first dose of double-blind medication in Study 1, a positive orthostatic test result at 4 hours post dose was observed in 7% of patients (37 of 498) who received FLOMAX capsules 0.4 mg once daily and in 3% of the patients (8 of 253) who received placebo. At 8 hours post dose, a positive orthostatic test result was observed for 6% of the patients (31 of 498) who received FLOMAX capsules 0.4 mg once daily and 4% (9 of 250) who received placebo (Note: patients in the 0.8 mg group received 0.4 mg once daily for the first week of Study 1).

In Studies 1 and 2, at least one positive orthostatic test result was observed during the course of these studies for 81 of the 502 patients (16%) in the FLOMAX capsules 0.4 mg once-daily group, 92 of the 491 patients (19%) in the FLOMAX capsules 0.8 mg once-daily group, and 54 of the 493 patients (11%) in the placebo group.

Because orthostasis was detected more frequently in FLOMAX capsule-treated patients than in placebo recipients, there is a potential risk of syncope [see Warnings and Precautions (5.1)].

Abnormal Ejaculation

Abnormal ejaculation includes ejaculation failure, ejaculation disorder, retrograde ejaculation, and ejaculation decrease. As shown in Table 1, abnormal ejaculation was associated with FLOMAX capsules administration and was dose-related in the U.S. studies. Withdrawal from these clinical studies of FLOMAX capsules because of abnormal ejaculation was also dose-dependent, with 8 of 492 patients (1.6%) in the 0.8 mg group and no patients in the 0.4 mg or placebo groups discontinuing treatment due to abnormal ejaculation.

Laboratory Tests

No laboratory test interactions with FLOMAX capsules are known. Treatment with FLOMAX capsules for up to 12 months had no significant effect on prostate-specific antigen (PSA).

6.2 Postmarketing Experience

The following adverse reactions have been identified during postapproval use of FLOMAX capsules. Because these reactions are reported voluntarily from a population of uncertain size, it is not always possible to reliably estimate their frequency or establish a causal relationship to drug exposure. Decisions to include these reactions in labeling are typically based on one or more of the following factors: (1) seriousness of the reaction, (2) frequency of reporting, or (3) strength of causal connection to FLOMAX capsules.

Allergic-type reactions such as skin rash, urticaria, pruritus, angioedema, and respiratory symptoms have been reported with positive rechallenge in some cases. Priapism has been reported rarely. Infrequent reports of dyspnea, palpitations, hypotension, atrial fibrillation, arrhythmia, tachycardia, skin desquamation including reports of Stevens-Johnson syndrome, erythema multiforme, dermatitis exfoliative, constipation, vomiting, dry mouth, visual impairment, and epistaxis have been received during the postmarketing period.

During cataract and glaucoma surgery, a variant of small pupil syndrome known as Intraoperative Floppy Iris Syndrome (IFIS) has been reported in association with alpha1 blocker therapy [see Warnings and Precautions (5.5)].

7 DRUG INTERACTIONS

7.1 Cytochrome P450 Inhibition

Strong and Moderate Inhibitors of CYP3A4 or CYP2D6

Tamsulosin is extensively metabolized, mainly by CYP3A4 and CYP2D6.

Concomitant treatment with ketoconazole (a strong inhibitor of CYP3A4) resulted in an increase in the Cmax and AUC of tamsulosin by a factor of 2.2 and 2.8, respectively [see Warnings and Precautions (5.2) and Clinical Pharmacology (12.3)]. The effects of concomitant administration of a moderate CYP3A4 inhibitor (e.g., erythromycin) on the pharmacokinetics of FLOMAX have not been evaluated [see Warnings and Precautions (5.2) and Clinical Pharmacology (12.3)].

Concomitant treatment with paroxetine (a strong inhibitor of CYP2D6) resulted in an increase in the Cmax and AUC of tamsulosin by a factor of 1.3 and 1.6, respectively [see Warnings and Precautions (5.2) and Clinical Pharmacology (12.3)]. A similar increase in exposure is expected in CYP2D6 poor metabolizers (PM) as compared to extensive metabolizers (EM). Since CYP2D6 PMs cannot be readily identified and the potential for significant increase in tamsulosin exposure exists when FLOMAX 0.4 mg is coadministered with strong CYP3A4 inhibitors in CYP2D6 PMs, FLOMAX capsules 0.4 mg should not be used in combination with strong inhibitors of CYP3A4 (e.g., ketoconazole) [see Warnings and Precautions (5.2) and Clinical Pharmacology (12.3)].

The effects of concomitant administration of a moderate CYP2D6 inhibitor (e.g., terbinafine) on the pharmacokinetics of FLOMAX have not been evaluated [see Warnings and Precautions (5.2) and Clinical Pharmacology (12.3)].

The effects of coadministration of both a CYP3A4 and a CYP2D6 inhibitor with FLOMAX capsules have not been evaluated. However, there is a potential for significant increase in tamsulosin exposure when FLOMAX 0.4 mg is coadministered with a combination of both CYP3A4 and CYP2D6 inhibitors [see Warnings and Precautions (5.2) and Clinical Pharmacology (12.3)].

Cimetidine

Treatment with cimetidine resulted in a significant decrease (26%) in the clearance of tamsulosin hydrochloride, which resulted in a moderate increase in tamsulosin hydrochloride AUC (44%) [see Warnings and Precautions (5.2) and Clinical Pharmacology (12.3)].

7.2 Other Alpha Adrenergic Blocking Agents

The pharmacokinetic and pharmacodynamic interactions between FLOMAX capsules and other alpha adrenergic blocking agents have not been determined; however, interactions between FLOMAX capsules and other alpha adrenergic blocking agents may be expected [see Warnings and Precautions (5.2) and Clinical Pharmacology (12.3)].

7.3 PDE5 Inhibitors

Caution is advised when alpha adrenergic blocking agents including FLOMAX are coadministered with PDE5 inhibitors. Alpha-adrenergic blockers and PDE5 inhibitors are both vasodilators that can lower blood pressure. Concomitant use of these two drug classes can potentially cause symptomatic hypotension [see Warnings and Precautions (5.2) and Clinical Pharmacology (12.3)].

7.4 Warfarin

A definitive drug-drug interaction study between tamsulosin hydrochloride and warfarin was not conducted. Results from limited in vitro and in vivo studies are inconclusive. Caution should be exercised with concomitant administration of warfarin and FLOMAX capsules [see Warnings and Precautions (5.2) and Clinical Pharmacology (12.3)].

7.5 Nifedipine, Atenolol, Enalapril

Dosage adjustments are not necessary when FLOMAX capsules are administered concomitantly with nifedipine, atenolol, or enalapril [see Clinical Pharmacology (12.3)].

7.6 Digoxin and Theophylline

Dosage adjustments are not necessary when a FLOMAX capsule is administered concomitantly with digoxin or theophylline [see Clinical Pharmacology (12.3)].

7.7 Furosemide

FLOMAX capsules had no effect on the pharmacodynamics (excretion of electrolytes) of furosemide. While furosemide produced an 11% to 12% reduction in tamsulosin hydrochloride Cmax and AUC, these changes are expected to be clinically insignificant and do not require adjustment of the FLOMAX capsules dosage [see Clinical Pharmacology (12.3)].

8 USE IN SPECIFIC POPULATIONS

8.1 Pregnancy

Risk Summary

FLOMAX is not indicated for use in women. There are no adequate data on the developmental risk associated with the use of FLOMAX in pregnant women. No adverse developmental effects were observed in animal studies in which tamsulosin hydrochloride was administered to rats or rabbits during the period of organogenesis (GD 7 to 17 in the rat and GD 6 to 18 in the rabbit) [see Data].

In the U.S. general population, the estimated background risk of major birth defects and of miscarriage in clinically recognized pregnancies is 2%–4% and 15%–20%, respectively.

Data

Administration of tamsulosin hydrochloride to pregnant female rats during the period of organogenesis at dose levels up to approximately 50 times the human therapeutic AUC exposure (300 mg/kg/day) revealed no evidence of harm to the fetus. Administration of tamsulosin hydrochloride to pregnant rabbits during the period of organogenesis at dose levels up to 50 mg/kg/day produced no evidence of fetal harm.

8.2 Lactation

FLOMAX is not indicated for use in women. There are no data on the presence of tamsulosin hydrochloride in human milk, the effects of tamsulosin hydrochloride on the breastfed infant, or the effects of tamsulosin hydrochloride on milk production. Tamsulosin hydrochloride is present in the milk of lactating rats [see Data].

Data

Oral administration of radiolabeled tamsulosin hydrochloride to rats demonstrated that tamsulosin hydrochloride and/or its metabolites are excreted into the milk of rats.

8.3 Females and Males of Reproductive Potential

Infertility

Males

Abnormal ejaculation including ejaculation failure, ejaculation disorder, retrograde ejaculation, and ejaculation decrease has been associated with FLOMAX [see Adverse Reactions (6.1)]. Studies in rats revealed significantly reduced fertility in males considered to be due to impairment of ejaculation, which was reversible [see Nonclinical Toxicology (13.1)].

Females

FLOMAX is not indicated for use in women. Female fertility in rats was significantly reduced, considered to be due to impairment of fertilization [see Nonclinical Toxicology (13.1)].

8.4 Pediatric Use

FLOMAX capsules are not indicated for use in pediatric populations.

Efficacy and positive benefit/risk of tamsulosin hydrochloride was not demonstrated in two studies conducted in patients 2 years to 16 years of age with elevated detrusor leak point pressure (>40 cm H2O) associated with known neurological disorder (e.g., spina bifida). Patients in both studies were treated on a weight-based mg/kg schema (0.025 mg, 0.05 mg, 0.1 mg, 0.2 mg, or 0.4 mg tamsulosin hydrochloride) for the reduction in detrusor leak point pressure below 40 cm H2O. In a randomized, double-blind, placebo-controlled, 14-week, pharmacokinetic, safety and efficacy study in 161 patients, no statistically significant difference in the proportion of responders was observed between groups receiving tamsulosin hydrochloride and placebo. In an open-label, 12-month safety study, 87 patients were treated with tamsulosin hydrochloride. The most frequently reported adverse events (≥5%) from the pooled data of both studies were urinary tract infection, vomiting, pyrexia, headache, nasopharyngitis, cough, pharyngitis, influenza, diarrhea, abdominal pain, and constipation.

8.5 Geriatric Use

Of the total number of subjects (1783) in clinical studies of tamsulosin, 36% were 65 years of age and over. No overall differences in safety or effectiveness were observed between these subjects and younger subjects, and the other reported clinical experience has not identified differences in responses between the elderly and younger patients, but greater sensitivity of some older individuals cannot be ruled out [see Clinical Pharmacology (12.3)].

8.6 Renal Impairment

Patients with renal impairment do not require an adjustment in FLOMAX capsules dosing. However, patients with end-stage renal disease (CLcr <10 mL/min/1.73 m^2) have not been studied [see Clinical Pharmacology (12.3)].

8.7 Hepatic Impairment

Patients with moderate hepatic impairment do not require an adjustment in FLOMAX capsules dosage. FLOMAX has not been studied in patients with severe hepatic impairment [see Clinical Pharmacology (12.3)].

10 OVERDOSAGE

Should overdosage of FLOMAX capsules lead to hypotension [see Warnings and Precautions (5.1) and Adverse Reactions (6.1)], support of the cardiovascular system is of first importance. Restoration of blood pressure and normalization of heart rate may be accomplished by keeping the patient in the supine position. If this measure is inadequate, then administration of intravenous fluids should be considered. If necessary, vasopressors should then be used and renal function should be monitored and supported as needed. Laboratory data indicate that tamsulosin hydrochloride is 94% to 99% protein bound; therefore, dialysis is unlikely to be of benefit.

11 DESCRIPTION

Tamsulosin hydrochloride is an antagonist of alpha1A adrenoceptors in the prostate.

Tamsulosin hydrochloride is (-)-(R)-5-[2-[[2-(o-Ethoxyphenoxy)ethyl]amino]propyl]-2-methoxybenzenesulfonamide, monohydrochloride. Tamsulosin hydrochloride is a white crystalline powder that melts with decomposition at approximately 230°C. It is sparingly soluble in water and methanol, slightly soluble in glacial acetic acid and ethanol, and practically insoluble in ether.

The empirical formula of tamsulosin hydrochloride is C20H28N2O5S ∙ HCl. The molecular weight of tamsulosin hydrochloride is 444.98. Its structural formula is:

Each FLOMAX capsule for oral administration contains tamsulosin hydrochloride, USP 0.4 mg, and the following inactive ingredients: microcrystalline cellulose; methacrylic acid copolymer dispersion; triacetin; calcium stearate; talc; gelatin; iron oxide; FD&C blue No. 2; titanium dioxide; propylene glycol; and shellac.

12 CLINICAL PHARMACOLOGY

12.1 Mechanism of Action

The symptoms associated with benign prostatic hyperplasia (BPH) are related to bladder outlet obstruction, which is comprised of two underlying components: static and dynamic. The static component is related to an increase in prostate size caused, in part, by a proliferation of smooth muscle cells in the prostatic stroma. However, the severity of BPH symptoms and the degree of urethral obstruction do not correlate well with the size of the prostate. The dynamic component is a function of an increase in smooth muscle tone in the prostate and bladder neck leading to constriction of the bladder outlet. Smooth muscle tone is mediated by the sympathetic nervous stimulation of alpha1 adrenoceptors, which are abundant in the prostate, prostatic capsule, prostatic urethra, and bladder neck. Blockade of these adrenoceptors can cause smooth muscles in the bladder neck and prostate to relax, resulting in an improvement in urine flow rate and a reduction in symptoms of BPH.

Tamsulosin, an alpha1 adrenoceptor blocking agent, exhibits selectivity for alpha1 receptors in the human prostate. At least three discrete alpha1 adrenoceptor subtypes have been identified: alpha1A, alpha1B, and alpha1D; their distribution differs between human organs and tissue. Approximately 70% of the alpha1 receptors in the human prostate are of the alpha1A subtype.

FLOMAX capsules are not intended for use as an antihypertensive drug.

12.2 Pharmacodynamics

Urologic pharmacodynamic effects have been evaluated in neurologically impaired pediatric patients and in adults with BPH [see Use in Specific Populations (8.4) and Clinical Studies (14)].

12.3 Pharmacokinetics

The pharmacokinetics of tamsulosin hydrochloride have been evaluated in adult healthy volunteers and patients with BPH after single and/or multiple administration with doses ranging from 0.1 mg to 1 mg.

Absorption

Absorption of tamsulosin hydrochloride from FLOMAX capsules 0.4 mg is essentially complete (>90%) following oral administration under fasting conditions. Tamsulosin hydrochloride exhibits linear kinetics following single and multiple dosing, with achievement of steady-state concentrations by the fifth day of once-a-day dosing.

Effect of Food

The time to maximum concentration (Tmax) is reached by 4 to 5 hours under fasting conditions and by 6 to 7 hours when FLOMAX capsules are administered with food. Taking FLOMAX capsules under fasted conditions results in a 30% increase in bioavailability (AUC) and 40% to 70% increase in peak concentrations (Cmax) compared to fed conditions (Figure 1).

Figure 1: Mean Plasma Tamsulosin Hydrochloride Concentrations Following Single-Dose Administration of FLOMAX Capsules 0.4 mg Under Fasted and Fed Conditions (n=8)

The effects of food on the pharmacokinetics of tamsulosin hydrochloride are consistent regardless of whether a FLOMAX capsule is taken with a light breakfast or a high-fat breakfast (Table 2).

Table 2: Mean (± S.D.) Pharmacokinetic Parameters Following FLOMAX Capsules 0.4 mg Once Daily or 0.8 mg Once Daily with a Light Breakfast, High-Fat Breakfast or Fasted
Pharmacokinetic Parameter | 0.4 mg QD to healthy volunteers; n=23 (age range 18–32 years) |  | 0.8 mg QD to healthy volunteers; n=22 (age range 55–75 years)
 | Light Breakfast | Fasted | Light Breakfast | High-Fat Breakfast | Fasted
Cmin (ng/mL) | 4.0 ± 2.6 | 3.8 ± 2.5 | 12.3 ± 6.7 | 13.5 ± 7.6 | 13.3 ± 13.3
Cmax (ng/mL) | 10.1 ± 4.8 | 17.1 ± 17.1 | 29.8 ± 10.3 | 29.1 ± 11.0 | 41.6 ± 15.6
Cmax/Cmin Ratio | 3.1 ± 1.0 | 5.3 ± 2.2 | 2.7 ± 0.7 | 2.5 ± 0.8 | 3.6 ± 1.1
Tmax (hours) | 6.0 | 4.0 | 7.0 | 6.6 | 5.0
T1/2 (hours) | - | - | - | - | 14.9 ± 3.9
AUCτ (ng∙hr/mL) | 151 ± 81.5 | 199 ± 94.1 | 440 ± 195 | 449 ± 217 | 557 ± 257
Cmin = observed minimum concentration
Cmax = observed maximum tamsulosin hydrochloride plasma concentration
Tmax = median time-to-maximum concentration
T1/2 = observed half-life
AUCτ = area under the tamsulosin hydrochloride plasma time curve over the dosing interval

Distribution

The mean steady-state apparent volume of distribution of tamsulosin hydrochloride after intravenous administration to 10 healthy male adults was 16 L, which is suggestive of distribution into extracellular fluids in the body.

Tamsulosin hydrochloride is extensively bound to human plasma proteins (94% to 99%), primarily alpha1 acid glycoprotein (AAG), with linear binding over a wide concentration range (20 to 600 ng/mL). The results of two-way in vitro studies indicate that the binding of tamsulosin hydrochloride to human plasma proteins is not affected by amitriptyline, diclofenac, glyburide, simvastatin plus simvastatin-hydroxy acid metabolite, warfarin, diazepam, propranolol, trichlormethiazide, or chlormadinone. Likewise, tamsulosin hydrochloride had no effect on the extent of binding of these drugs.

Metabolism

There is no enantiomeric bioconversion from tamsulosin hydrochloride [R(-) isomer] to the S(+) isomer in humans. Tamsulosin hydrochloride is extensively metabolized by cytochrome P450 enzymes in the liver and less than 10% of the dose is excreted in urine unchanged. However, the pharmacokinetic profile of the metabolites in humans has not been established. Tamsulosin is extensively metabolized, mainly by CYP3A4 and CYP2D6 as well as via some minor participation of other CYP isoenzymes. Inhibition of hepatic drug-metabolizing enzymes may lead to increased exposure to tamsulosin [see Warnings and Precautions (5.2) and Drug Interactions (7.1)]. The metabolites of tamsulosin hydrochloride undergo extensive conjugation to glucuronide or sulfate prior to renal excretion.

Incubations with human liver microsomes showed no evidence of clinically significant metabolic interactions between tamsulosin hydrochloride and amitriptyline, albuterol (beta agonist), glyburide (glibenclamide) and finasteride (5-alpha-reductase inhibitor for treatment of BPH). However, results of the in vitro testing of the tamsulosin hydrochloride interaction with diclofenac and warfarin were equivocal.

Excretion

On administration of the radiolabeled dose of tamsulosin hydrochloride to 4 healthy volunteers, 97% of the administered radioactivity was recovered, with urine (76%) representing the primary route of excretion compared to feces (21%) over 168 hours.

Following intravenous or oral administration of an immediate-release formulation, the elimination half-life of tamsulosin hydrochloride in plasma ranged from 5 to 7 hours. Because of absorption rate-controlled pharmacokinetics with FLOMAX capsules, the apparent half-life of tamsulosin hydrochloride is approximately 9 to 13 hours in healthy volunteers and 14 to 15 hours in the target population.

Tamsulosin hydrochloride undergoes restrictive clearance in humans, with a relatively low systemic clearance (2.88 L/h).

Specific Populations

Pediatric use

FLOMAX capsules are not indicated for use in pediatric populations [see Use in Specific Populations (8.4)].

Geriatric (age) use

Cross-study comparison of FLOMAX capsules overall exposure (AUC) and half-life indicates that the pharmacokinetic disposition of tamsulosin hydrochloride may be slightly prolonged in geriatric males compared to young, healthy male volunteers. Intrinsic clearance is independent of tamsulosin hydrochloride binding to AAG, but diminishes with age, resulting in a 40% overall higher exposure (AUC) in subjects of age 55 to 75 years compared to subjects of age 20 to 32 years [see Use in Specific Populations (8.5)].

Renal impairment

The pharmacokinetics of tamsulosin hydrochloride have been compared in 6 subjects with mild-moderate (30≤ CLcr <70 mL/min/1.73 m^2) or moderate-severe (10≤ CLcr <30 mL/min/1.73 m^2) renal impairment and 6 normal subjects (CLcr >90 mL/min/1.73 m^2). While a change in the overall plasma concentration of tamsulosin hydrochloride was observed as the result of altered binding to AAG, the unbound (active) concentration of tamsulosin hydrochloride, as well as the intrinsic clearance, remained relatively constant. Therefore, patients with renal impairment do not require an adjustment in FLOMAX capsules dosing. However, patients with end-stage renal disease (CLcr <10 mL/min/1.73 m^2) have not been studied [see Use in Specific Populations (8.6)].

Hepatic impairment

The pharmacokinetics of tamsulosin hydrochloride have been compared in 8 subjects with moderate hepatic impairment (Child-Pugh's classification: Grades A and B) and 8 normal subjects. While a change in the overall plasma concentration of tamsulosin hydrochloride was observed as the result of altered binding to AAG, the unbound (active) concentration of tamsulosin hydrochloride does not change significantly, with only a modest (32%) change in intrinsic clearance of unbound tamsulosin hydrochloride. Therefore, patients with moderate hepatic impairment do not require an adjustment in FLOMAX capsules dosage. FLOMAX has not been studied in patients with severe hepatic impairment [see Use in Specific Populations (8.7)].

Drug Interactions

Cytochrome P450 inhibition

Strong and moderate inhibitors of CYP3A4 or CYP2D6

The effects of ketoconazole (a strong inhibitor of CYP3A4) at 400 mg once daily for 5 days on the pharmacokinetics of a single FLOMAX capsule 0.4 mg dose was investigated in 24 healthy volunteers (age range 23 to 47 years). Concomitant treatment with ketoconazole resulted in an increase in the Cmax and AUC of tamsulosin by a factor of 2.2 and 2.8, respectively [see Warnings and Precautions (5.2) and Clinical Pharmacology (12.3)]. The effects of concomitant administration of a moderate CYP3A4 inhibitor (e.g., erythromycin) on the pharmacokinetics of FLOMAX have not been evaluated [see Warnings and Precautions (5.2) and Drug Interactions (7.1)].

The effects of paroxetine (a strong inhibitor of CYP2D6) at 20 mg once daily for 9 days on the pharmacokinetics of a single FLOMAX capsule 0.4 mg dose was investigated in 24 healthy volunteers (age range 23 to 47 years). Concomitant treatment with paroxetine resulted in an increase in the Cmax and AUC of tamsulosin by a factor of 1.3 and 1.6, respectively [see Warnings and Precautions (5.2) and Drug Interactions (7.1)]. A similar increase in exposure is expected in CYP2D6 poor metabolizers (PM) as compared to extensive metabolizers (EM). A fraction of the population (about 7% of Caucasians and 2% of African Americans) are CYP2D6 PMs. Since CYP2D6 PMs cannot be readily identified and the potential for significant increase in tamsulosin exposure exists when FLOMAX 0.4 mg is coadministered with strong CYP3A4 inhibitors in CYP2D6 PMs, FLOMAX capsules 0.4 mg should not be used in combination with strong inhibitors of CYP3A4 (e.g., ketoconazole) [see Warnings and Precautions (5.2) and Drug Interactions (7.1)].

The effects of concomitant administration of a moderate CYP2D6 inhibitor (e.g., terbinafine) on the pharmacokinetics of FLOMAX have not been evaluated [see Warnings and Precautions (5.2) and Drug Interactions (7.1)].

The effects of coadministration of both a CYP3A4 and a CYP2D6 inhibitor with FLOMAX capsules have not been evaluated. However, there is a potential for significant increase in tamsulosin exposure when FLOMAX 0.4 mg is coadministered with a combination of both CYP3A4 and CYP2D6 inhibitors [see Warnings and Precautions (5.2) and Drug Interactions (7.1)].

Cimetidine

The effects of cimetidine at the highest recommended dose (400 mg every 6 hours for 6 days) on the pharmacokinetics of a single FLOMAX capsule 0.4 mg dose was investigated in 10 healthy volunteers (age range 21 to 38 years). Treatment with cimetidine resulted in a significant decrease (26%) in the clearance of tamsulosin hydrochloride, which resulted in a moderate increase in tamsulosin hydrochloride AUC (44%) [see Warnings and Precautions (5.2) and Drug Interactions (7.1)].

Other alpha adrenergic blocking agents

The pharmacokinetic and pharmacodynamic interactions between FLOMAX capsules and other alpha adrenergic blocking agents have not been determined; however, interactions between FLOMAX capsules and other alpha adrenergic blocking agents may be expected [see Warnings and Precautions (5.2) and Drug Interactions (7.2)].

PDE5 inhibitors

Caution is advised when alpha adrenergic blocking agents, including FLOMAX, are coadministered with PDE5 inhibitors. Alpha-adrenergic blockers and PDE5 inhibitors are both vasodilators that can lower blood pressure. Concomitant use of these two drug classes can potentially cause symptomatic hypotension [see Warnings and Precautions (5.2) and Drug Interactions (7.3)].

Warfarin

A definitive drug-drug interaction study between tamsulosin hydrochloride and warfarin was not conducted. Results from limited in vitro and in vivo studies are inconclusive. Therefore, caution should be exercised with concomitant administration of warfarin and FLOMAX capsules [see Warnings and Precautions (5.2) and Drug Interactions (7.4)].

Nifedipine, atenolol, enalapril

In three studies in hypertensive subjects (age range 47 to 79 years) whose blood pressure was controlled with stable doses of nifedipine, atenolol, or enalapril for at least 3 months, FLOMAX capsules 0.4 mg for 7 days followed by FLOMAX capsules 0.8 mg for another 7 days (n=8 per study) resulted in no clinically significant effects on blood pressure and pulse rate compared to placebo (n=4 per study). Therefore, dosage adjustments are not necessary when FLOMAX capsules are administered concomitantly with nifedipine, atenolol, or enalapril [see Drug Interactions (7.5)].

Digoxin and theophylline

In two studies in healthy volunteers (n=10 per study; age range 19 to 39 years) receiving FLOMAX capsules 0.4 mg/day for 2 days, followed by FLOMAX capsules 0.8 mg/day for 5 to 8 days, single intravenous doses of digoxin 0.5 mg or theophylline 5 mg/kg resulted in no change in the pharmacokinetics of digoxin or theophylline. Therefore, dosage adjustments are not necessary when a FLOMAX capsule is administered concomitantly with digoxin or theophylline [see Drug Interactions (7.6)].

Furosemide

The pharmacokinetic and pharmacodynamic interaction between FLOMAX capsules 0.8 mg/day (steady-state) and furosemide 20 mg intravenously (single dose) was evaluated in 10 healthy volunteers (age range 21 to 40 years). FLOMAX capsules had no effect on the pharmacodynamics (excretion of electrolytes) of furosemide. While furosemide produced an 11% to 12% reduction in tamsulosin hydrochloride Cmax and AUC, these changes are expected to be clinically insignificant and do not require adjustment of the FLOMAX capsules dosage [see Drug Interactions (7.7)].

13 NONCLINICAL TOXICOLOGY

13.1 Carcinogenesis, Mutagenesis, Impairment of Fertility

Rats administered doses up to 43 mg/kg/day in males and 52 mg/kg/day in females had no increases in tumor incidence, with the exception of a modest increase in the frequency of mammary gland fibroadenomas in female rats receiving doses ≥5.4 mg/kg (P<0.015). The highest doses of tamsulosin hydrochloride evaluated in the rat carcinogenicity study produced systemic exposures (AUC) in rats 3 times the exposures in men receiving the maximum therapeutic dose of 0.8 mg/day.

Mice were administered doses up to 127 mg/kg/day in males and 158 mg/kg/day in females. There were no significant tumor findings in male mice. Female mice treated for 2 years with the two highest doses of 45 and 158 mg/kg/day had statistically significant increases in the incidence of mammary gland fibroadenomas (P<0.0001) and adenocarcinomas (P<0.0075). The highest dose levels of tamsulosin hydrochloride evaluated in the mice carcinogenicity study produced systemic exposures (AUC) in mice 8 times the exposures in men receiving the maximum therapeutic dose of 0.8 mg/day.

The increased incidences of mammary gland neoplasms in female rats and mice were considered secondary to tamsulosin hydrochloride-induced hyperprolactinemia. It is not known if FLOMAX capsules elevate prolactin in humans. The relevance for human risk of the findings of prolactin-mediated endocrine tumors in rodents is not known.

Tamsulosin hydrochloride produced no evidence of mutagenic potential in vitro in the Ames reverse mutation test, mouse lymphoma thymidine kinase assay, unscheduled DNA repair synthesis assay, and chromosomal aberration assays in Chinese hamster ovary cells or human lymphocytes. There were no mutagenic effects in the in vivo sister chromatid exchange and mouse micronucleus assay.

Studies in rats revealed significantly reduced fertility in males dosed with single or multiple daily doses of 300 mg/kg/day of tamsulosin hydrochloride (AUC exposure in rats about 50 times the human exposure with the maximum therapeutic dose). The mechanism of decreased fertility in male rats is considered to be an effect of the compound on the vaginal plug formation possibly due to changes of semen content or impairment of ejaculation. The effects on fertility were reversible, showing improvement by 3 days after a single dose and 4 weeks after multiple dosing. Effects on fertility in males were completely reversed within nine weeks of discontinuation of multiple dosing. Multiple doses of 10 and 100 mg/kg/day tamsulosin hydrochloride (1/5 and 16 times the anticipated human AUC exposure) did not significantly alter fertility in male rats. Effects of tamsulosin hydrochloride on sperm counts or sperm function have not been evaluated.

Studies in female rats revealed significant reductions in fertility after single or multiple dosing with 300 mg/kg/day of the R-isomer or racemic mixture of tamsulosin hydrochloride, respectively. In female rats, the reductions in fertility after single doses were considered to be associated with impairments in fertilization. Multiple dosing with 10 or 100 mg/kg/day of the racemic mixture did not significantly alter fertility in female rats.

14 CLINICAL STUDIES

Four placebo-controlled clinical studies and one active-controlled clinical study enrolled a total of 2296 patients (1003 received FLOMAX capsules 0.4 mg once daily, 491 received FLOMAX capsules 0.8 mg once daily, and 802 were control patients) in the U.S. and Europe.

In the two U.S. placebo-controlled, double-blind, 13-week, multicenter studies (Study 1 [US92-03A] and Study 2 [US93-01]), 1486 men with the signs and symptoms of BPH were enrolled. In both studies, patients were randomized to either placebo, FLOMAX capsules 0.4 mg once daily, or FLOMAX capsules 0.8 mg once daily. Patients in FLOMAX capsules 0.8 mg once-daily treatment groups received a dose of 0.4 mg once daily for one week before increasing to the 0.8 mg once-daily dose. The primary efficacy assessments included: 1) total American Urological Association (AUA) Symptom Score questionnaire, which evaluated irritative (frequency, urgency, and nocturia), and obstructive (hesitancy, incomplete emptying, intermittency, and weak stream) symptoms, where a decrease in score is consistent with improvement in symptoms; and 2) peak urine flow rate, where an increased peak urine flow rate value over baseline is consistent with decreased urinary obstruction.

Mean changes from baseline to Week 13 in total AUA Symptom Score were significantly greater for groups treated with FLOMAX capsules 0.4 mg and 0.8 mg once daily compared to placebo in both U.S. studies (Table 3, Figures 2A and 2B). The changes from baseline to Week 13 in peak urine flow rate were also significantly greater for the FLOMAX capsules 0.4 mg and 0.8 mg once-daily groups compared to placebo in Study 1, and for the FLOMAX capsules 0.8 mg once-daily group in Study 2 (Table 3, Figures 3A and 3B). Overall there were no significant differences in improvement observed in total AUA Symptom Scores or peak urine flow rates between the 0.4 mg and the 0.8 mg dose groups with the exception that the 0.8 mg dose in Study 1 had a significantly greater improvement in total AUA Symptom Score compared to the 0.4 mg dose.

Table 3: Mean (±S.D.) Changes from Baseline to Week 13 in Total AUA Symptom Score [Total AUA Symptom Scores ranged from 0 to 35.] and Peak Urine Flow Rate (mL/sec)
 | Total AUA Symptom Score |  | Peak Urine Flow Rate
 | Mean Baseline Value | Mean Change | Mean Baseline Value | Mean Change
Study 1 [Peak urine flow rate measured 4 to 8 hours post dose at Week 13.]
FLOMAX capsules 0.8 mg once daily | 19.9 ± 4.9 n=247 | -9.6 [Statistically significant difference from placebo (p-value ≤0.050; Bonferroni-Holm multiple test procedure).] ± 6.7 n=237 | 9.57 ± 2.51 n=247 | 1.78 ± 3.35 n=247
FLOMAX capsules 0.4 mg once daily | 19.8 ± 5.0 n=254 | -8.3 ± 6.5 n=246 | 9.46 ± 2.49 n=254 | 1.75 ± 3.57 n=254
Placebo | 19.6 ± 4.9 n=254 | -5.5 ± 6.6 n=246 | 9.75 ± 2.54 n=254 | 0.52 ± 3.39 n=253
Study 2 [Peak urine flow rate measured 24 to 27 hours post dose at Week 13.]
FLOMAX capsules 0.8 mg once daily | 18.2 ± 5.6 n=244 | -5.8 ± 6.4 n=238 | 9.96 ± 3.16 n=244 | 1.79 ± 3.36 n=237
FLOMAX capsules 0.4 mg once daily | 17.9 ± 5.8 n=248 | -5.1 ± 6.4 n=244 | 9.94 ± 3.14 n=248 | 1.52 ± 3.64 n=244
Placebo | 19.2 ± 6.0 n=239 | -3.6 ± 5.7 n=235 | 9.95 ± 3.12 n=239 | 0.93 ± 3.28 n=235
Week 13: For patients not completing the 13-week study, the last observation was carried forward.

Mean total AUA Symptom Scores for both FLOMAX capsules 0.4 mg and 0.8 mg once-daily groups showed a rapid decrease starting at 1 week after dosing and remained decreased through 13 weeks in both studies (Figures 2A and 2B).

In Study 1, 400 patients (53% of the originally randomized group) elected to continue in their originally assigned treatment groups in a double-blind, placebo-controlled, 40-week extension trial (138 patients on 0.4 mg, 135 patients on 0.8 mg, and 127 patients on placebo). Three hundred twenty-three patients (43% of the originally randomized group) completed one year. Of these, 81% (97 patients) on 0.4 mg, 74% (75 patients) on 0.8 mg, and 56% (57 patients) on placebo had a response ≥25% above baseline in total AUA Symptom Score at one year.

Figure 2A: Mean Change from Baseline in Total AUA Symptom Score (0–35) Study 1

* indicates significant difference from placebo (p-value ≤0.050).
B = Baseline determined approximately one week prior to the initial dose of double-blind medication at Week 0.
Subsequent values are observed cases.
LOCF = Last observation carried forward for patients not completing the 13-week study.
Note: Patients in the 0.8 mg treatment group received 0.4 mg for the first week.
Note: Total AUA Symptom Scores range from 0 to 35.

Figure 2B: Mean Change from Baseline in Total AUA Symptom Score (0–35) Study 2

* indicates significant difference from placebo (p-value ≤0.050).
Baseline measurement was taken Week 0. Subsequent values are observed cases.
LOCF = Last observation carried forward for patients not completing the 13-week study.
Note: Patients in the 0.8 mg treatment group received 0.4 mg for the first week.
Note: Total AUA Symptom Scores range from 0 to 35.

Figure 3A: Mean Increase in Peak Urine Flow Rate (mL/Sec) Study 1

* indicates significant difference from placebo (p-value ≤0.050).
B = Baseline determined approximately one week prior to the initial dose of double-blind medication at Week 0.
Subsequent values are observed cases.
LOCF = Last observation carried forward for patients not completing the 13-week study.
Note: The uroflowmetry assessments at Week 0 were recorded 4 to 8 hours after patients received the first dose of double-blind medication.
Measurements at each visit were scheduled 4 to 8 hours after dosing (approximate peak plasma tamsulosin concentration).
Note: Patients in the 0.8 mg treatment groups received 0.4 mg for the first week.

Figure 3B: Mean Increase in Peak Urine Flow Rate (mL/Sec) Study 2

* indicates significant difference from placebo (p-value ≤0.050).
Baseline measurement was taken Week 0. Subsequent values are observed cases.
LOCF = Last observation carried forward for patients not completing the 13-week study.
Note: Patients in the 0.8 mg treatment group received 0.4 mg for the first week.
Note: Week 1 and Week 2 measurements were scheduled 4 to 8 hours after dosing (approximate peak plasma tamsulosin concentration).
All other visits were scheduled 24 to 27 hours after dosing (approximate trough tamsulosin concentration).

16 HOW SUPPLIED/STORAGE AND HANDLING

FLOMAX capsules 0.4 mg are supplied in high density polyethylene bottles containing 100 hard gelatin capsules with olive green opaque cap and orange opaque body. The capsules are imprinted on one side with Flomax 0.4 mg and on the other side with BI 58.

FLOMAX capsules 0.4 mg, 100 capsules (NDC 0024-5837-01)

STORAGE AND HANDLING

Store at 25°C (77°F); excursions permitted to 15°C–30°C (59°F–86°F) [see USP Controlled Room Temperature].

Keep FLOMAX capsules and all medicines out of reach of children.

17 PATIENT COUNSELING INFORMATION

Advise the patient to read the FDA-approved patient labeling (Patient Information).

• Hypotension

Advise the patient about the possible occurrence of symptoms related to postural hypotension, such as dizziness, when taking FLOMAX capsules, and they should be cautioned about driving, operating machinery, or performing hazardous tasks [see Warnings and Precautions (5.1)].

• Drug Interactions

Advise the patient that FLOMAX should not be used in combination with strong inhibitors of CYP3A4 [see Warnings and Precautions (5.2) and Drug Interactions (7.1)].

• Priapism

Advise the patient about the possibility of priapism as a result of treatment with FLOMAX capsules and other similar medications. Patients should be informed that this reaction is extremely rare, but if not brought to immediate medical attention, can lead to permanent erectile dysfunction (impotence) [see Warnings and Precautions (5.3)].

• Screening for Prostate Cancer

Prostate cancer and BPH frequently coexist; therefore, screen patients for the presence of prostate cancer prior to treatment with FLOMAX capsules and at regular intervals afterwards [see Warnings and Precautions (5.4)].

• Intraoperative Floppy Iris Syndrome

Advise the patient when considering cataract or glaucoma surgery to tell their ophthalmologist that they have taken FLOMAX capsules [see Warnings and Precautions (5.5)].

• Administration

Advise the patient that FLOMAX capsules should not be crushed, chewed or opened [see Dosage and Administration (2)].

FDA-approved Patient Labeling

Patient labeling is provided as a tear-off leaflet at the end of this prescribing information.

Distributed by:
sanofi-aventis U.S. LLC
Bridgewater, NJ 08807
A SANOFI COMPANY

Flomax is a registered trademark of and licensed from:
Astellas Pharma Inc.
Tokyo 103-8411, JAPAN

© 2019. All rights reserved.

PATIENT INFORMATION

Flomax® (Flō-max)
(tamsulosin hydrochloride, USP)
Capsules, 0.4 mg

Read the Patient Information that comes with FLOMAX capsules before you start taking it and each time you refill your prescription. The information may have changed. This leaflet does not take the place of discussions with your doctor about your medical condition or your treatment.

What is FLOMAX?

FLOMAX is a prescription alpha-blocker medicine used to treat the signs and symptoms of benign prostatic hyperplasia (BPH), a condition your doctor may refer to as an enlarged prostate.

- FLOMAX is not for women.
- FLOMAX is not for children.

Who should not take FLOMAX?

Do not take FLOMAX capsules if you are allergic to any of its ingredients. See the end of this leaflet for a complete list of ingredients in FLOMAX capsules.

What should I tell my doctor before using FLOMAX?

Before taking FLOMAX capsules, tell your doctor about all your medical conditions, including:

- any kidney or liver problems.
- any history of low blood pressure.
- any allergies to sulfa or any other medicines.
- if you are planning to have cataract or glaucoma surgery.

Tell your doctor about all the medicines you take, including:

- any prescription medicines, including blood pressure medicines.
- any non-prescription medicines, including vitamins and herbal supplements.

Some of your other medicines may affect the way FLOMAX capsules work. Especially tell your doctor if you take a medicine for high blood pressure. You should not take FLOMAX if you are already taking certain blood pressure medicines.

Know the medicines you take. Keep a list of them and show it to your doctor and pharmacist when you get a new medicine.

How should I take FLOMAX?

- Take FLOMAX exactly as prescribed by your doctor.
- Do not crush, chew, or open FLOMAX capsules.
- Take FLOMAX one time each day, about 30 minutes after the same meal each day. For example, you may take FLOMAX 30 minutes after dinner each day.
- If you miss a dose of FLOMAX, take it as soon as you remember. If you miss your dose for the whole day, continue with your next dose on your regular schedule. Do not take two doses at the same time.
- If you stop or forget to take FLOMAX for several days, talk with your doctor before starting again.
- If you take more FLOMAX capsules than prescribed, call your doctor right away.

What are the possible side effects of FLOMAX capsules?

Possible side effects of FLOMAX may include:

- Decreased blood pressure when changing positions. FLOMAX capsules may cause a sudden drop in blood pressure upon standing, especially after the first dose or when changing doses.
  Symptoms may include:
    - fainting
    - dizziness
    - lightheadedness
  Change positions slowly from lying down to sitting up or from a sitting to a standing position until you learn how you react to FLOMAX capsules. If you begin to feel dizzy, sit or lie down until you feel better. If the symptoms are severe or do not improve, call your doctor.
- Allergic reactions. Make your doctor aware of any allergic reactions you may experience while taking FLOMAX.
  Allergic reactions may include:
    - rash
    - itching
    - hives
  Rare and more serious allergic reactions may also occur. Get medical help right away if you have any of the following reactions:
    - swelling of face, tongue, or throat
    - difficulty breathing
    - blistering of the skin
- A painful erection that will not go away. FLOMAX capsules can cause a painful erection (priapism), which cannot be relieved by having sex. If this happens, get medical help right away. If priapism is not treated, you may not be able to get an erection in the future.
- Eye problems during cataract or glaucoma surgery. During cataract or glaucoma surgery, a condition called intraoperative floppy iris syndrome (IFIS) can happen if you take or have taken FLOMAX capsules. If you need to have cataract or glaucoma surgery, be sure to tell your surgeon if you take or have taken FLOMAX capsules.

Common side effects of FLOMAX capsules may include:

- runny nose
- dizziness
- decreased semen

These are not all the possible side effects with FLOMAX capsules. Tell your doctor if you have any side effect that bothers you or that does not go away.

Call your doctor for medical advice about side effects. You may report side effects to FDA at 1-800-FDA-1088, or by visiting www.fda.gov/medwatch.

What should I avoid while taking FLOMAX capsules?

Avoid driving, operating machinery, or other dangerous activities, until you know how FLOMAX affects you. FLOMAX capsules may cause a sudden drop in blood pressure upon standing, especially after the first dose or when changing doses. See "What are the possible side effects of FLOMAX capsules?"

How do I store FLOMAX capsules?

Store FLOMAX capsules at Room Temperature 68°F to 77°F (20°C to 25°C). Short-term exposure to higher or lower temperatures (from 59°F [15°C] to 86°F [30°C]) is acceptable. Ask your doctor or pharmacist if you have any questions about storing your capsules.

Keep FLOMAX capsules and all medicines out of the reach of children.

General information

This medicine was prescribed for you by your doctor for your condition. Do not use it for another condition. Do not give FLOMAX to other people, even if they have the same symptoms that you have. It may harm them.

While taking FLOMAX, you must have regular checkups. Follow your doctor's advice about when to have these checkups.

BPH can occur with other more serious conditions, including prostate cancer. Therefore, ask your doctor about screening for prostate cancer prior to treatment with FLOMAX capsules and at regular intervals afterwards.

This patient information leaflet summarizes the most important information about FLOMAX. If you would like more information, talk with your doctor. You can ask your pharmacist or doctor for information about FLOMAX that is written for health professionals. For current prescribing information, access www.4flomax.com or call sanofi-aventis U.S. LLC at 1-800-633-1610.

What are the ingredients in FLOMAX capsules?

- Active Ingredient: tamsulosin hydrochloride, USP
- Inactive Ingredients: microcrystalline cellulose; methacrylic acid copolymer dispersion; triacetin; calcium stearate; talc; gelatin; iron oxide; FD&C blue No. 2; titanium dioxide; propylene glycol; and shellac.

Distributed by:
sanofi-aventis U.S. LLC
Bridgewater, NJ 08807
A SANOFI COMPANY

Flomax is a registered trademark of and licensed from:
Astellas Pharma Inc.
Tokyo 103-8411, JAPAN

© 2019. All rights reserved.

This Patient Information has been approved by the U.S. Food and Drug Administration.

Revised: January 2019

PRINCIPAL DISPLAY PANEL - 0.4 mg Capsule Bottle Label

NDC 0024-5837-01

Flomax ®
(tamsulosin
hydrochloride)

0.4 mg
100 capsules

Rx only

Dosage: Read accompanying
prescribing information.

SANOFI